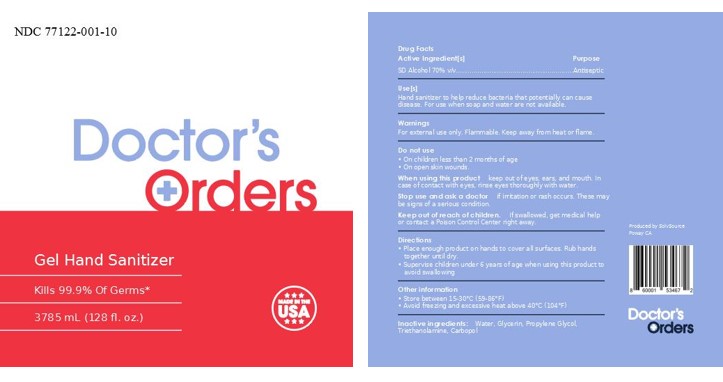 DRUG LABEL: hand sanitizer gel
NDC: 77122-001 | Form: GEL
Manufacturer: the california spirits company
Category: otc | Type: HUMAN OTC DRUG LABEL
Date: 20200610

ACTIVE INGREDIENTS: ALCOHOL 70 mL/100 mL
INACTIVE INGREDIENTS: TROLAMINE 0.1 mL/100 mL; WATER 25 mL/100 mL; CARBOMER INTERPOLYMER TYPE B (ALLYL PENTAERYTHRITOL CROSSLINKED) 0.4 mL/100 mL; GLYCERIN 2.5 mL/100 mL; PROPYLENE GLYCOL 4 mL/100 mL

hand sanitizer gel

Active Ingredient(s)

SD Alcohol 70% v/v.

Purpose

Antiseptic

Use

Hand Sanitizer to help reduce bacteria that potentially can cause disease. For use when soap and water are not available.

Warnings

For external use only. Flammable. Keep away from heat or flame

Do not use

- on children less than 2 months of age
- on open skin wounds

When using this product keep out of eyes, ears, and mouth. In case of contact with eyes, rinse eyes thoroughly with water.

Stop use and ask a doctor if irritation or rash occurs. These may be signs of a serious condition.

Keep out of reach of children. If swallowed, get medical help or contact a Poison Control Center right away.

Directions

- Place enough product on hands to cover all surfaces. Rub hands together until dry.
- Supervise children under 6 years of age when using this product to avoid swallowing.

Other information

- Store between 15-30C (59-86F)
- Avoid freezing and excessive heat above 40C (104F)

Inactive ingredients

Water, Glycerin, Propylene Glycol, Triethanolamine, Carbopol

Package Label - Principal Display Panel

NDC: 77122-001-10